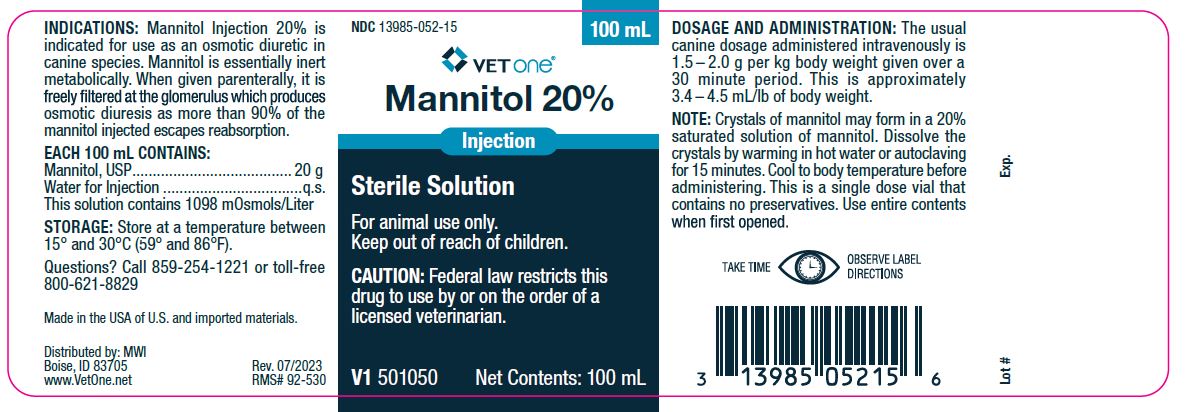 DRUG LABEL: Mannitol 20%
NDC: 13985-052 | Form: INJECTION
Manufacturer: MWI (VetOne)
Category: animal | Type: PRESCRIPTION ANIMAL DRUG LABEL
Date: 20240513

ACTIVE INGREDIENTS: MANNITOL 20 g/100 mL
INACTIVE INGREDIENTS: WATER

VetOne
MANNITOL 20%

INDICATIONS:

Mannitol Injection 20% is indicated for use as an osmotic diuretic in canine species. Mannitol is essentially inert metabolically. When given parenterally, it is freely filtered at the glomerulus which produces osmotic diuresis as more than 90% of the mannitol injected escapes reabsorption.

Each 100 mL Contains:

Mannitol USP...................................20 g

Water for Injection...........................q.s.

This solution contains 1098 m0smols/Liter

Dosage and Administration:

The usual canine dosage administered intravenously is 1.5 - 2.0 g per Kg body weight given over a 30 minute period. This is approximately 3.4-4.5 mL/lb of body weight.

Note:

Crystals of mannitol may form in a 20% saturated solution of mannitol. Dissolve the crystals by warming in hot water or autoclaving for 15 minutes. Cool to body temperature before administering. This is a single dose vial that contains no preservatives. Use entire contents when first opened.

Storage:

Store at temperatures between 15°and 30°C (59°-86°F)

Made in the USA of U.S. and imported materials.

Distributed by:

MWI

Boise, ID 83705

www.VetOne.net

WARNINGS AND PRECAUTIONS

Caution: Federal law restricts this drug to use by or on the order of a licensed veterinarian.

FOR ANIMAL USE ONLY

KEEP OUT OF THE REACH OF CHILDREN

Questions? Call 859-254-1221 or toll-free 800-621-8829

PACKAGE LABEL

NDC 13985-052-15

VETONE

Mannitol 20%

Injection

Sterile Solution

For animal use only.

Keep out of reach of children.

CAUTION: Federal law restricts this drug to use by ot on the order of a licensed veterinarian.

V1 501050

Net Contents: 100mL